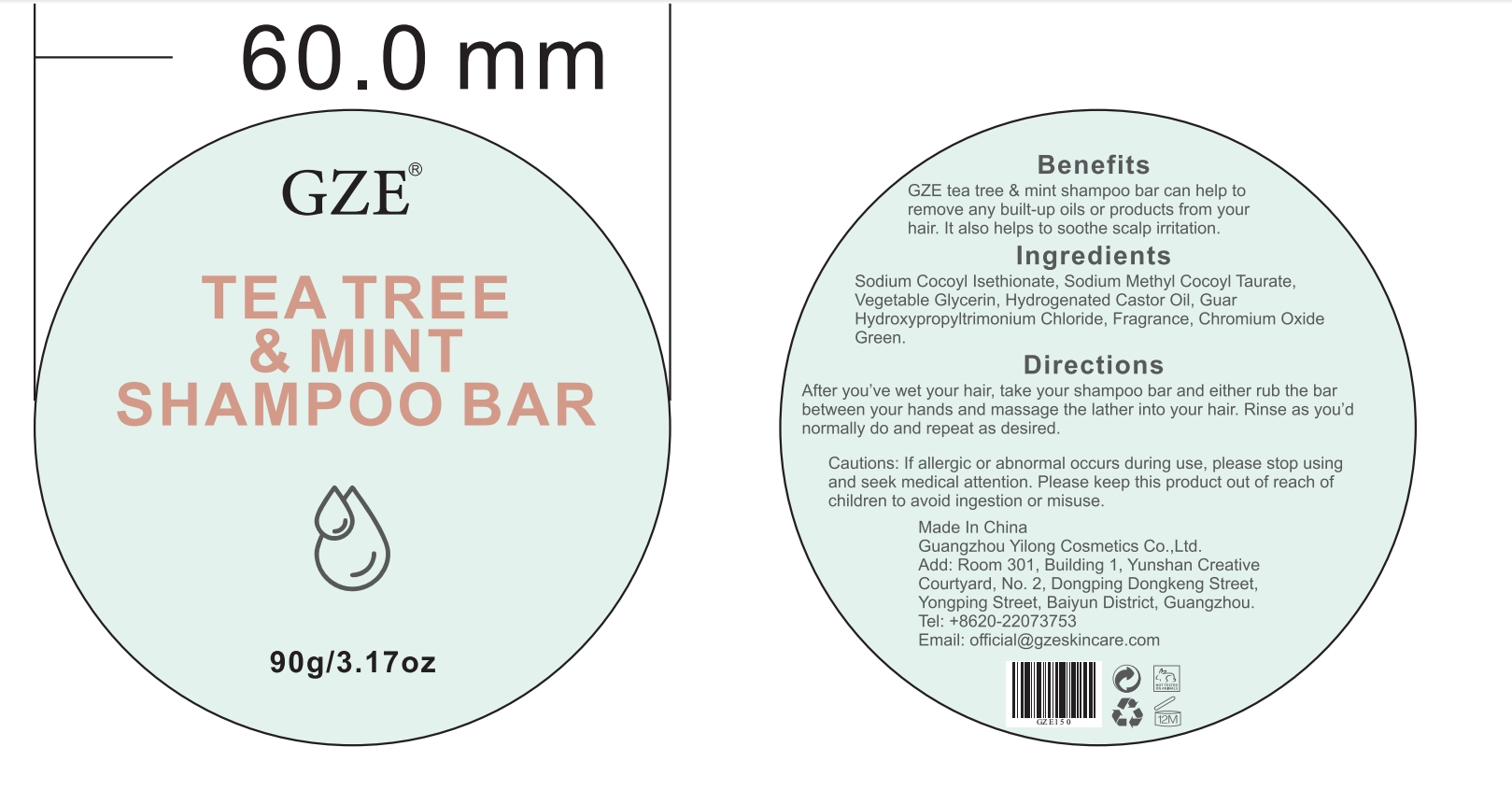 DRUG LABEL: GZE Tea Tree Mint ShampooBar
NDC: 74458-150 | Form: SOAP
Manufacturer: Guangzhou Yilong Cosmetics Co., Ltd
Category: otc | Type: HUMAN OTC DRUG LABEL
Date: 20241014

ACTIVE INGREDIENTS: HYDROGENATED CASTOR OIL 8 g/100 g
INACTIVE INGREDIENTS: SODIUM COCOYL ISETHIONATE; FRAGRANCE 13576; GUAR HYDROXYPROPYLTRIMONIUM CHLORIDE; SODIUM METHYL COCOYL TAURATE; CHROMIC OXIDE; GLYCERIN

GZE TEA TREE MINT SHAMPOO BAR

INACTIVE INGREDIENT

Sodium Cocoyl Isethionate

Sodium Methyl Cocoyl Taurate

Glycerin

Guar Hydroxypropyltrimonium Chloride

Fragrance

Chromium Oxide Green

ACTIVE INGREDIENT

Hydrogenated Castor Oil

PURPOSE

Clean Hair and sclap.

INDICATIONS AND USAGE

After you've wet your hair, take your shampoo bar and either rub the bar between your hands and massage the lather into your hair. Rinse as you'd normally do and repeat as desired.

WARNINGS

For external use only.

Stop use and ask a doctor if rash occurs.

Do not use on damaged or broken skin.

When using this product keep out of eyes. Rinse with water to remove.

Keep out of reach of children. If swallowed, get medical help or contact a Poison Control Center right away.

DOSAGE AND ADMINISTRATION

After you've wet your hair, take your shampoo bar and either rub the bar between your hands and massage the lather into your hair. Rinse as you'd normally do and repeat as desired.